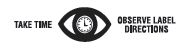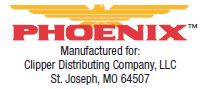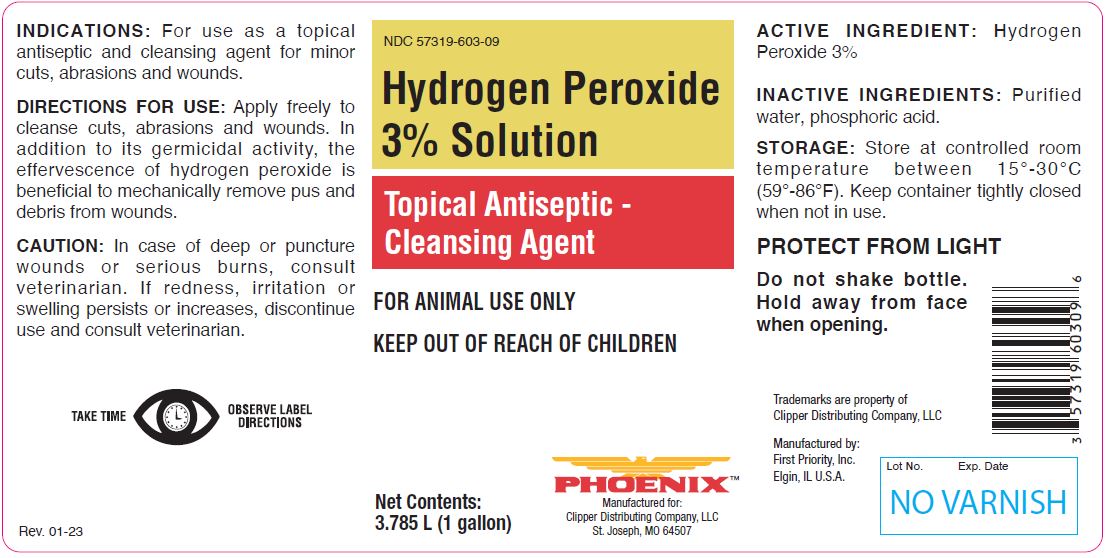 DRUG LABEL: Hydrogen Peroxide
NDC: 57319-603 | Form: SOLUTION
Manufacturer: Clipper Distributing Company, LLC
Category: animal | Type: OTC ANIMAL DRUG LABEL
Date: 20230321

ACTIVE INGREDIENTS: HYDROGEN PEROXIDE 59.2 g/1 L

Hydrogen Peroxide 3% Solution

PURPOSE

Topical Antiseptic - Cleansing Agent

KEEP OUT OF REACH OF CHILDREN

FOR ANIMAL USE ONLY
KEEP OUT OF REACH OF CHILDREN

Net Contents:

3.785 L (1 gallon)

INDICATIONS:

For use as a topical antiseptic and cleansing agent for minor cuts, abrasions and wounds.

DIRECTIONS FOR USE:

Apply freely to cleanse cuts, abrasions and wounds. In addition to its germicidal activity, the effervescence of hydrogen peroxide is beneficial to mechanically remove pus and debris from wounds.

CAUTION:

In case of deep or puncture wounds or serious burns, consult veterinarian. If redness, irritation, or swelling persists or increases, discontinue use and consult veterinarian.

Rev. 01-23

ACTIVE INGREDIENT:

Hydrogen Peroxide 3%

INACTIVE INGREDIENTS:

Purified water, phosphoric acid.

STORAGE:

Store at controlled room temperature between 15º to 30ºC (59º-86ºF). Keep container tightly closed when not in use.

PROTECT FROM LIGHT.

Do not shake bottle. Hold away from face when opening.

INFORMATION FOR OWNERS/CAREGIVERS

Trademarks are property of Clipper Distributing Company, LLC

Manufactured by:
First Priority, Inc.
Elgin, IL U.S.A.